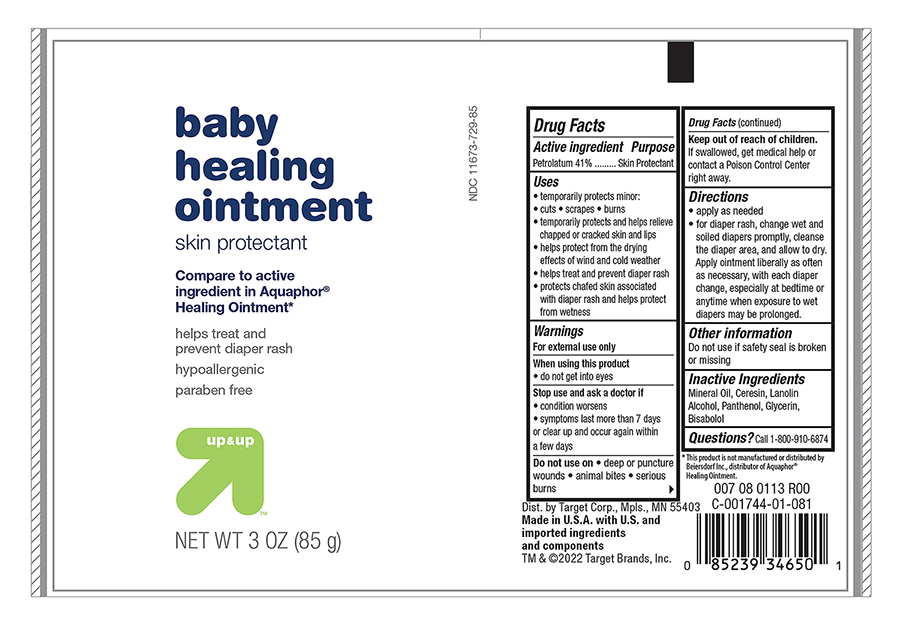 DRUG LABEL: Target Baby Healing
NDC: 11673-729 | Form: OINTMENT
Manufacturer: Target Corporation
Category: otc | Type: HUMAN OTC DRUG LABEL
Date: 20241121

ACTIVE INGREDIENTS: PETROLATUM 410 mg/1 g
INACTIVE INGREDIENTS: LIGHT MINERAL OIL; CERESIN; LANOLIN ALCOHOLS; GLYCERIN; PANTHENOL; LEVOMENOL

Active ingredient

Petrolatum - 41%

Purpose

Skin Protectant

Uses

• temporarily protects minor:

• cuts • scrapes • burns

• temporarily protects and helps relieve chapped or cracked skin and lips

• helps protect from the drying effects of wind and cold weather

• helps treat and prevent diaper rash

• protects chafed skin associated with diaper rash and helps protect from wetness

Directions

- apply as needed
- for diaper rash, use change wet or soiled diapers promptly cleanse the diaper area, and allow to dry.Apply ointment liberally as often as nessary, with each diaper change, especially at bedtime or anytime when exposed to wet diapers may be prolonged

Warnings

For External use only

When using this product

• do not get into eyes

Stop use and ask a doctor if

- conditions worsens
- symptoms last more than 7 days or clear up an occur again within a few days

Do not use on

- deep punture wounds
- animal bites
- serious burns

Keep out of the reach of children

If swallowed, get medical help
or contact a Poison Control Center right away.

Inactive ingredients:

Mineral Oil, Ceresin, Lanolin Alcohol, Panthenol, Glycerin, Bisabolol

Other information

Do not use if safety seal is broken

Principal primary panel -Tube

Target Up and Up NDC 11673-729-85

Baby Healing ointment

Petrolatum 41% Skin protectant

NET WT 3.0 OZ (85g)